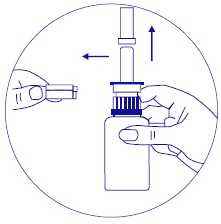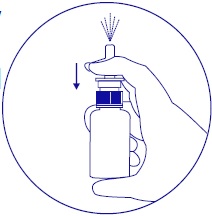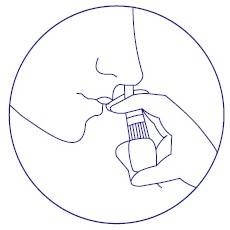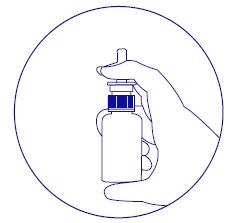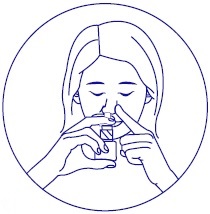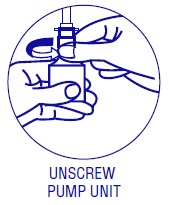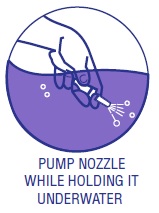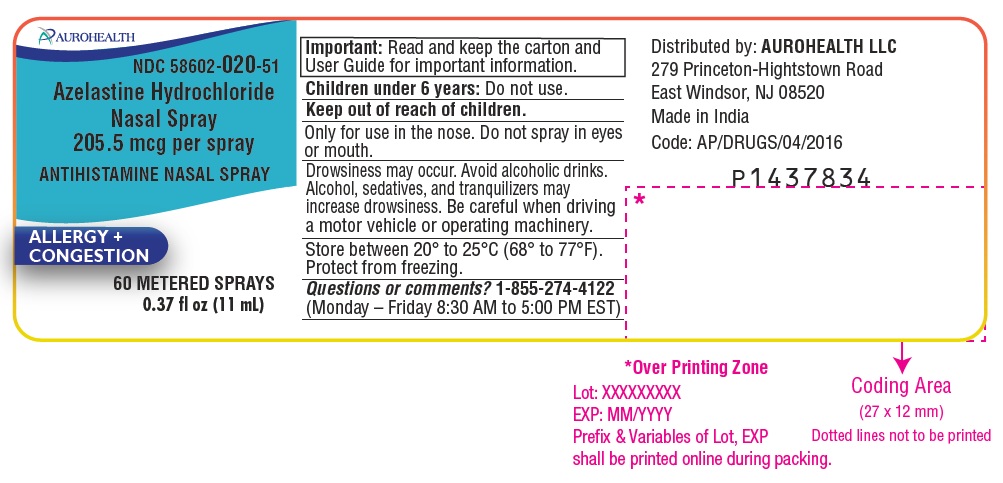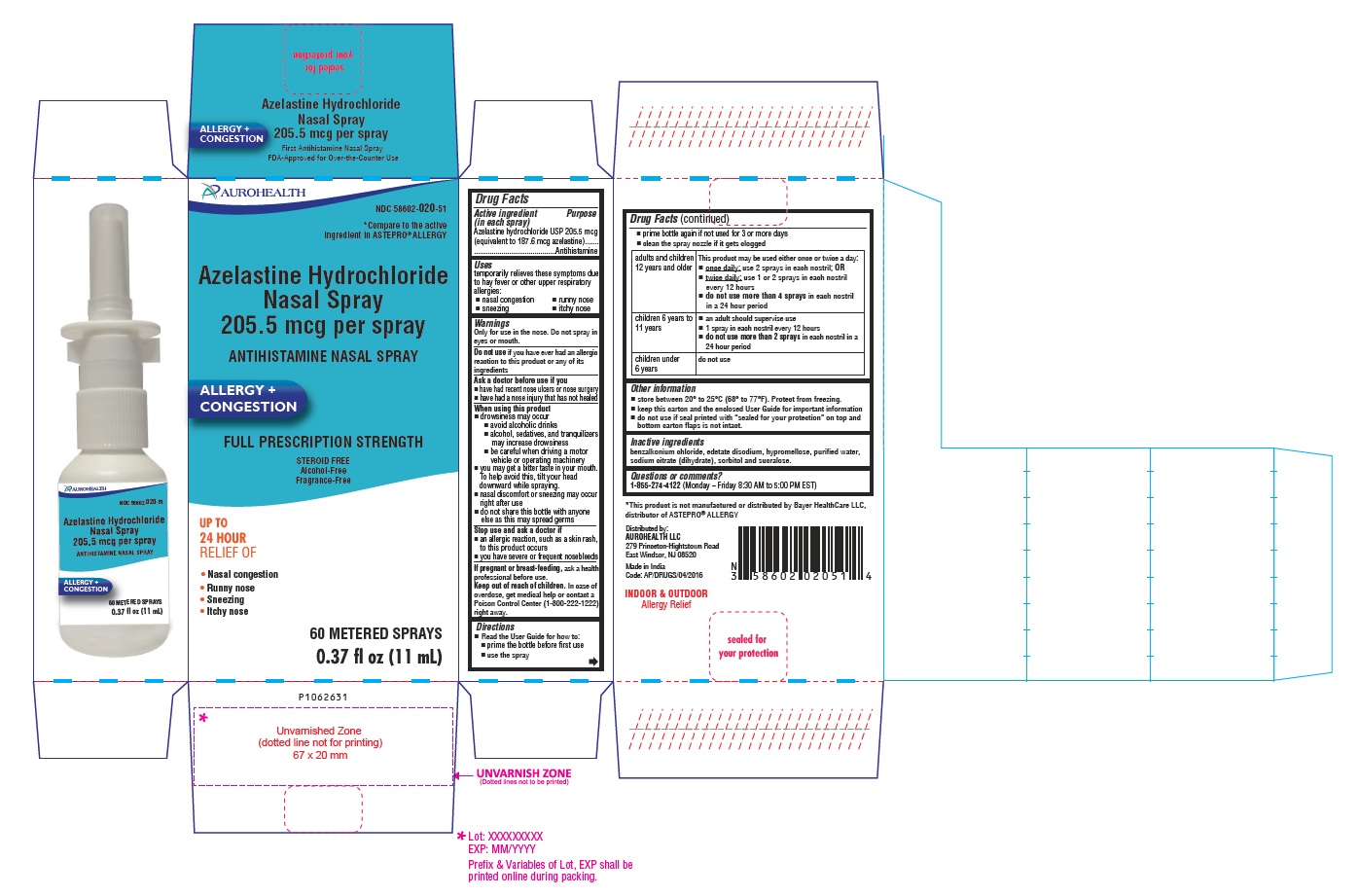 DRUG LABEL: AZELASTINE HYDROCHLORIDE
NDC: 58602-020 | Form: SPRAY, METERED
Manufacturer: Aurohealth LLC
Category: otc | Type: Human OTC Drug Label
Date: 20251215

ACTIVE INGREDIENTS: AZELASTINE HYDROCHLORIDE 205.5 ug/1 1
INACTIVE INGREDIENTS: BENZALKONIUM CHLORIDE; EDETATE DISODIUM; HYPROMELLOSE 2910 (4000 MPA.S); WATER; TRISODIUM CITRATE DIHYDRATE; SORBITOL; SUCRALOSE

Azelastine Hydrochloride Nasal Spray 205.5 mcg per spray

Drug Facts

Active ingredient (in each spray)

Azelastine hydrochloride USP 205.5 mcg (equivalent to 187.6 mcg azelastine)

Purpose

Antihistamine

Uses

temporarily relieves these symptoms due to hay fever or other upper respiratory allergies:

■ nasal congestion ■ runny nose ■ sneezing ■ itchy nose

Warnings

Only for use in the nose. Do not spray in eyes or mouth.

Do not use

if you have ever had an allergic reaction to this product or any of its ingredients

Ask a doctor before use if you

■ have had recent nose ulcers or nose surgery
■ have had a nose injury that has not healed

When using this product

■ drowsiness may occur
■ avoid alcoholic drinks
■ alcohol, sedatives, and tranquilizers may increase drowsiness
■ be careful when driving a motor vehicle or operating machinery

■ you may get a bitter taste in your mouth. To help avoid this, tilt your head downward while spraying.

■ nasal discomfort or sneezing may occur right after use

■ do not share this bottle with anyone else as this may spread germs

Stop use and ask a doctor if

■ an allergic reaction, such as a skin rash, to this product occurs
■ you have severe or frequent nosebleeds

If pregnant or breast-feeding,

ask a health professional before use.

Keep out of reach of children.

In case of overdose, get medical help or contact a Poison Control Center (1-800-222-1222) right away.

Directions

■ Read the User Guide for how to:

■ prime the bottle before first use ■ use the spray

■ prime bottle again if not used for 3 or more days ■ clean the spray nozzle if it gets clogged

adults and children 12 years and older | This product may be used either once or twice a day: ■ once daily: use 2 sprays in each nostril; OR ■ twice daily: use 1 or 2 sprays in each nostril every 12 hours ■ do not use more than 4 sprays in each nostril in a 24 hour period
children 6 years to 11 years | ■ an adult should supervise use ■ 1 spray in each nostril every 12 hours ■ do not use more than 2 sprays in each nostril in a 24 hour period
children under 6 years | do not use

Other information

- store between 20° to 25°C (68° to 77°F). Protect from freezing.
- keep this carton and the enclosed User Guide for important information
- do not use if seal printed with “sealed for your protection” on top and bottom carton flaps is not intact.

Inactive ingredients

benzalkonium chloride, edetate disodium, hypromellose, purified water, sodium citrate (dihydrate), sorbitol and sucralose.

Questions or comments? 1-855-274-4122 (Monday – Friday 8:30 AM to 5:00 PM EST)

Distributed by:
AUROHEALTH LLC
279 Princeton-Hightstown Road
East Windsor, NJ 08520
Made in India
Code: AP/DRUGS/04/2016

User Guide

Azelastine Hydrochloride Nasal Spray 205.5 mcg per spray

HOW TO START GETTING STEROID-FREE ALLERGY RELIEF RIGHT NOW

This User Guide will give you detailed directions on how to prime the bottle, use the spray, and how to clean a clogged nozzle.

Keep this User Guide as it contains important information.

GET THE BOTTLE READY

Remove the transparent cap and white clip before using.

PRIME THE BOTTLE

WHEN TO PRIME

- Before you use Azelastine Hydrochloride Nasal Spray for the first time
- If you have not used Azelastine Hydrochloride Nasal Spray for 3 or more days
- After you clean a clogged nozzle

HOW TO PRIME

• Aim bottle away from face.

• Hold bottle as shown and pump until a fine mist appears.
• If a fine mist does not appear after 6 sprays, your nozzle may be clogged. Please see “How to Clean a Clogged Nozzle” section.

HOW TO USE

Important: For use in your nose only

STEP 1

Blow your nose to clear your nostrils.

STEP 2

Tilt your head downward toward your toes.
TILT HEAD DOWNWARD
STEP 3

Hold bottle with thumb under bottle and spray nozzle between fingers.
STEP 4

Close one nostril.
HOLD ONE NOSTRIL SHUT
STEP 5

Put the spray tip about ¼ inch to ½ inch into the other nostril. Hold bottle upright and aim the spray tip toward the back of your nose.

STEP 6

While sniffing gently, press the pump once or twice (according to dosing directions found in Table 1).

Repeat Steps 4, 5 and 6 in other nostril.

STEP 7

Do not tilt your head back immediately after using Azelastine Hydrochloride Nasal Spray. This will help to keep the medicine from going into your throat, which may cause a bitter taste.

STEP 8

When you finish using your Azelastine Hydrochloride Nasal Spray, wipe the spray tip with a clean tissue or cloth. Put the clip and cap back on the bottle.

FOR USE IN CHILDREN

An adult should supervise use.

(See Steps 1 through 8).

SELECT THE DOSE

DIRECTIONS

Do not use more than directed

TABLE 1

adults & children 12 years and older | This product may be used either once or twice a day: ■ once daily: use 2 sprays in each nostril; OR ■ twice daily: use 1 or 2 sprays in each nostril every 12 hours ■ do not use more than 4 sprays in each nostril in a 24 hour period
children 6 years to 11 years | ■ an adult should supervise use ■ 1 spray in each nostril every 12 hours ■ do not use more than 2 sprays in each nostril in a 24 hour period
children under 6 years | do not use

IMPORTANT INFORMATION FOR USE

Remember, when using this product:

• Drowsiness may occur*

› Avoid alcoholic drinks.

› Alcohol, sedatives, and tranquilizers may increase drowsiness.

› Be careful when driving a motor vehicle or operating machinery.

*In clinical trials, drowsiness was observed in less than 4% of patients taking Azelastine Hydrochloride Nasal Spray.

HOW TO CLEAN A CLOGGED NOZZLE

If you cannot get your Azelastine Hydrochloride Nasal Spray to spray a fine mist, the nozzle may be clogged. Don’t try to unclog the nozzle with a pin or sharp object—that can damage it.

- Unscrew the spray pump unit from the bottle by turning it to the left (counter-clockwise).

- Keep open bottle out of reach of children.
- Fill a bowl or container with warm water. Soak only the spray pump unit in the warm water. Pump the nozzle several times while holding it under the water to clear the clog.

- Let the spray pump unit air dry before putting it back on.
- Tightly screw pump unit back on the open bottle by turning clockwise (to the right).
- After cleaning, follow the instructions for priming.

QUESTIONS OR COMMENTS? 1-855-274-4122 (Monday – Friday 8:30 AM to 5:00 PM EST)

Distributed by:
AUROHEALTH LLC
279 Princeton-Hightstown Road
East Windsor, NJ 08520
Made in India
Code: AP/DRUGS/04/2016
Revised: 01/2024

PACKAGE LABEL-PRINCIPAL DISPLAY PANEL - Container Label (11 mL Bottle)

AUROHEALTH
NDC 58602-020-51
Azelastine Hydrochloride
Nasal Spray
205.5 mcg per spray
ANTIHISTAMINE NASAL SPRAY
ALLERGY +
CONGESTION
60 METERED SPRAYS
0.37 fl oz (11 mL)

PACKAGE LABEL-PRINCIPAL DISPLAY PANEL - Container Carton Label (11 mL Bottle)

AUROHEALTH
NDC 58602-020-51
*Compare to the active
ingredient in ASTEPRO® ALLERGY
Azelastine Hydrochloride
Nasal Spray
205.5 mcg per spray
ANTIHISTAMINE NASAL SPRAY
ALLERGY +
CONGESTION
FULL PRESCRIPTION STRENGTH
STEROID FREE
Alcohol-Free
Fragrance-Free
UP TO
24 HOUR
RELIEF OF
• Nasal congestion
• Runny nose
• Sneezing
• Itchy nose
60 METERED SPRAYS
0.37 fl oz (11 mL)